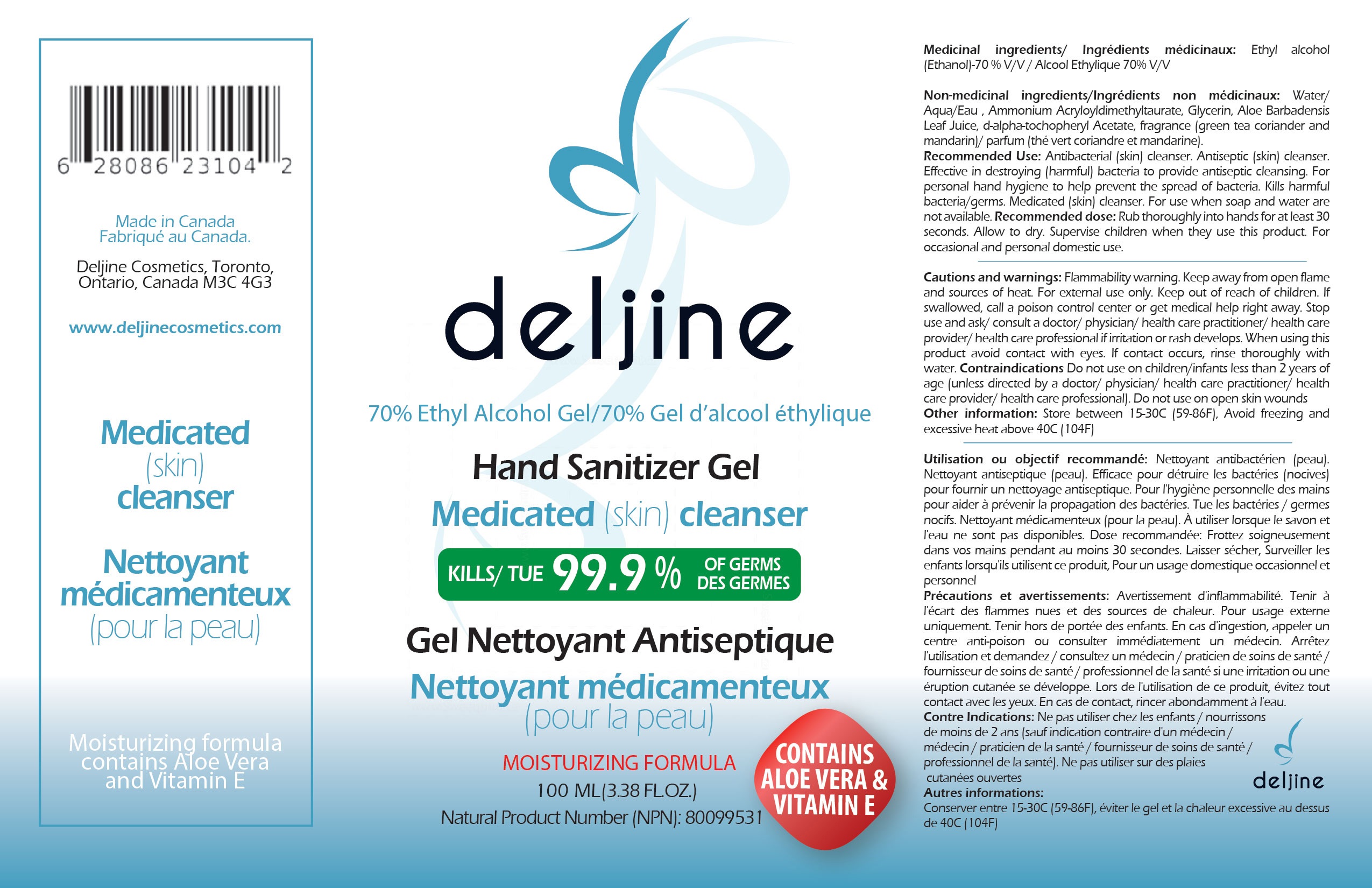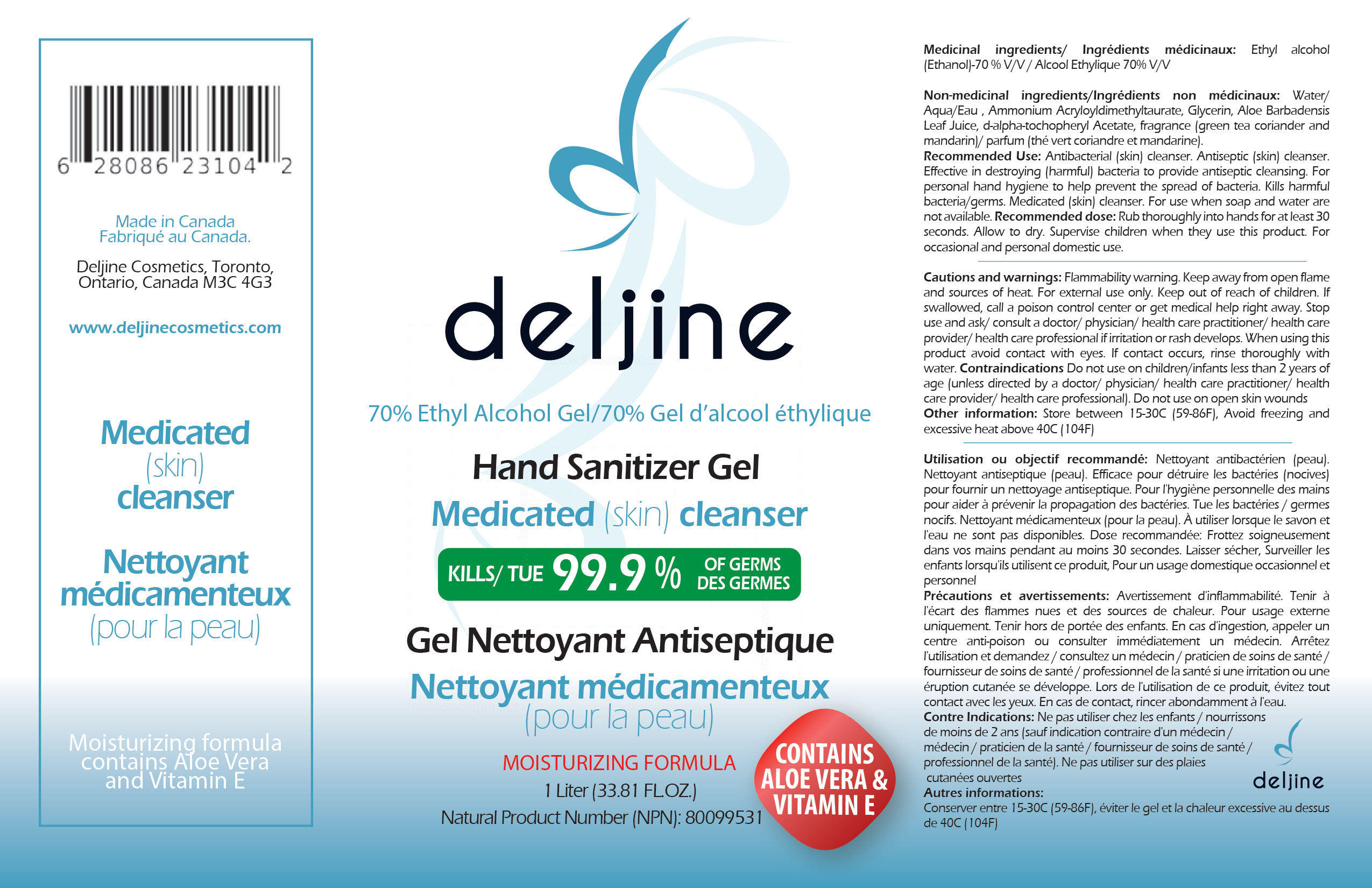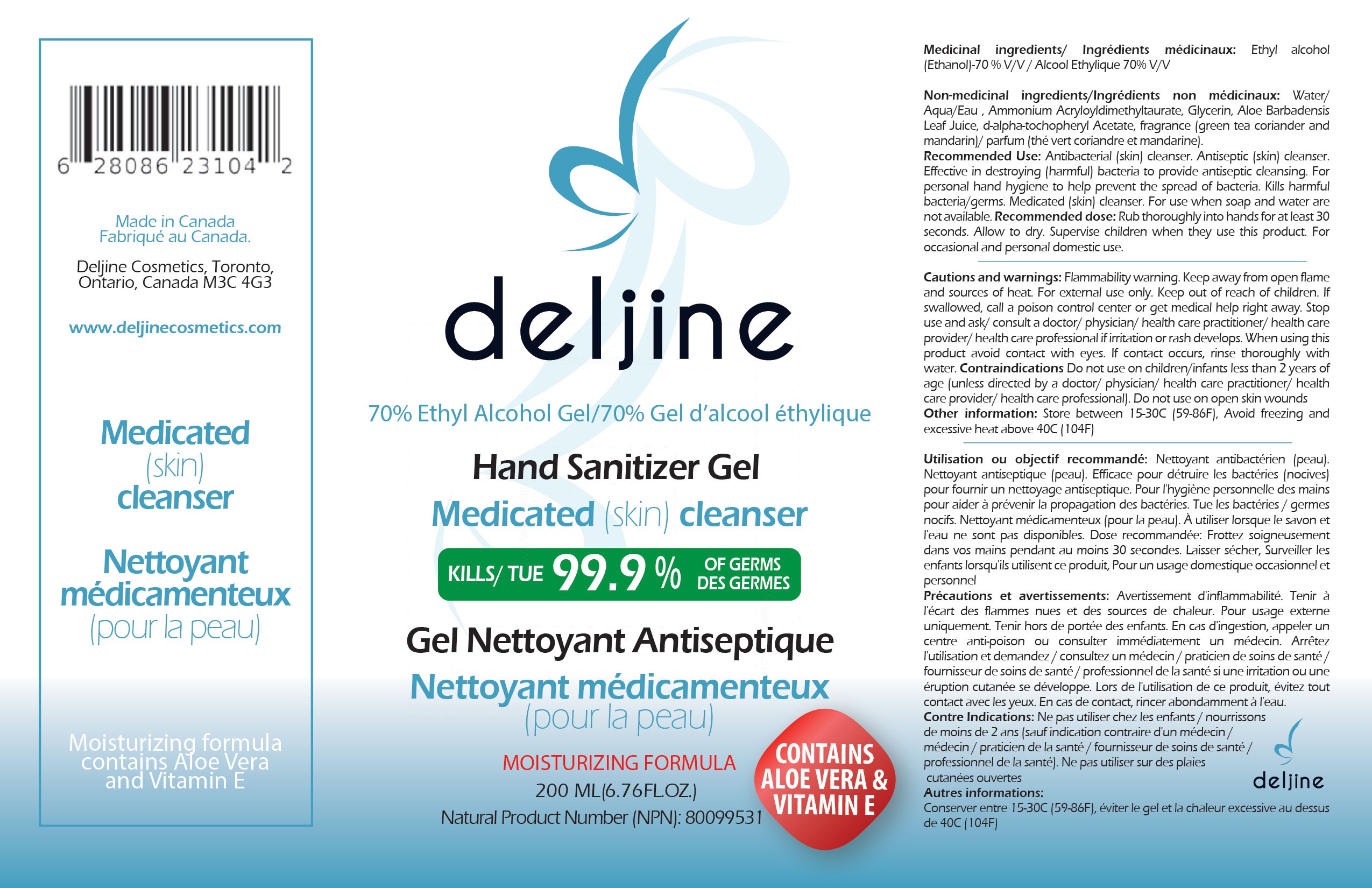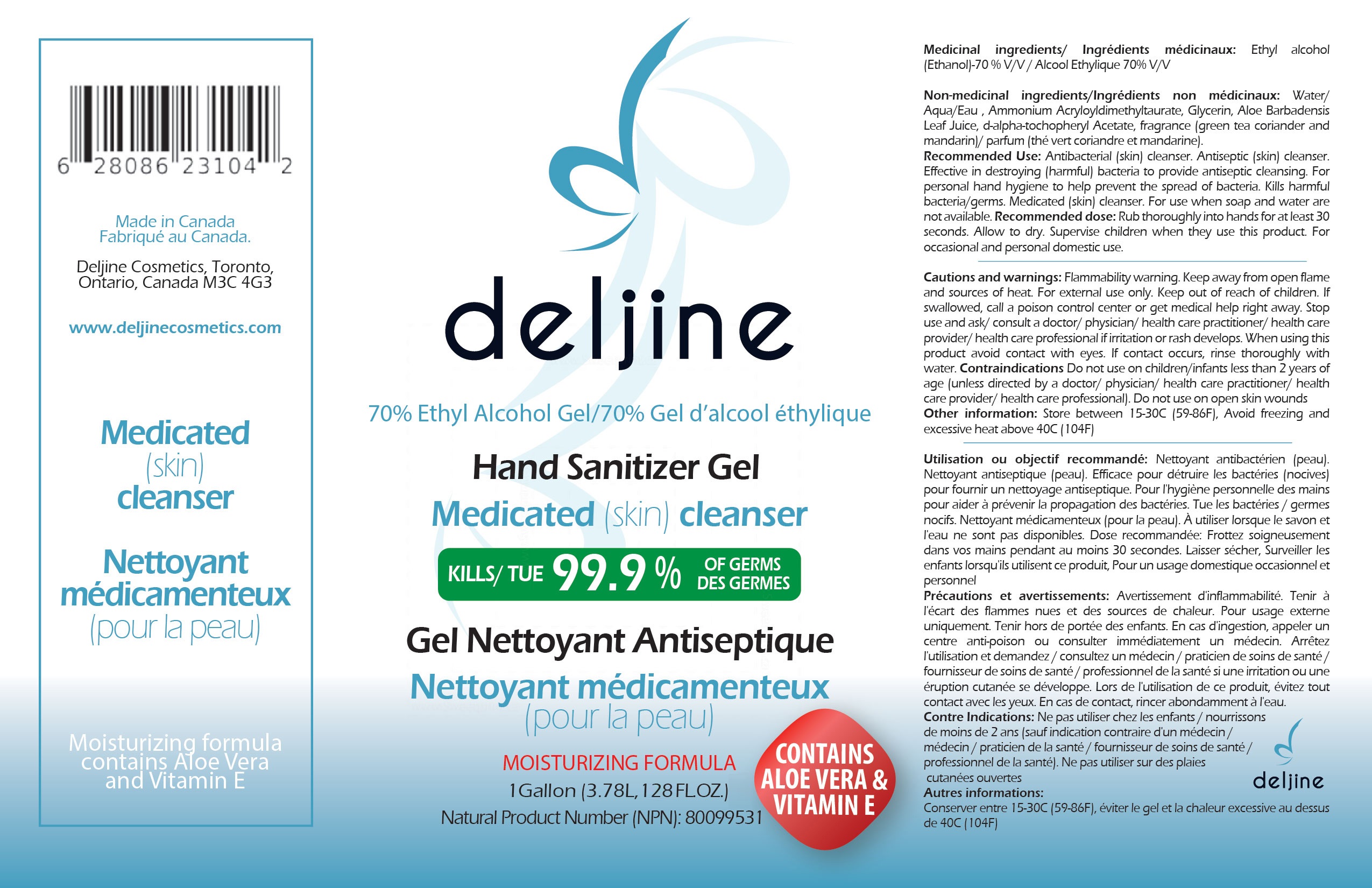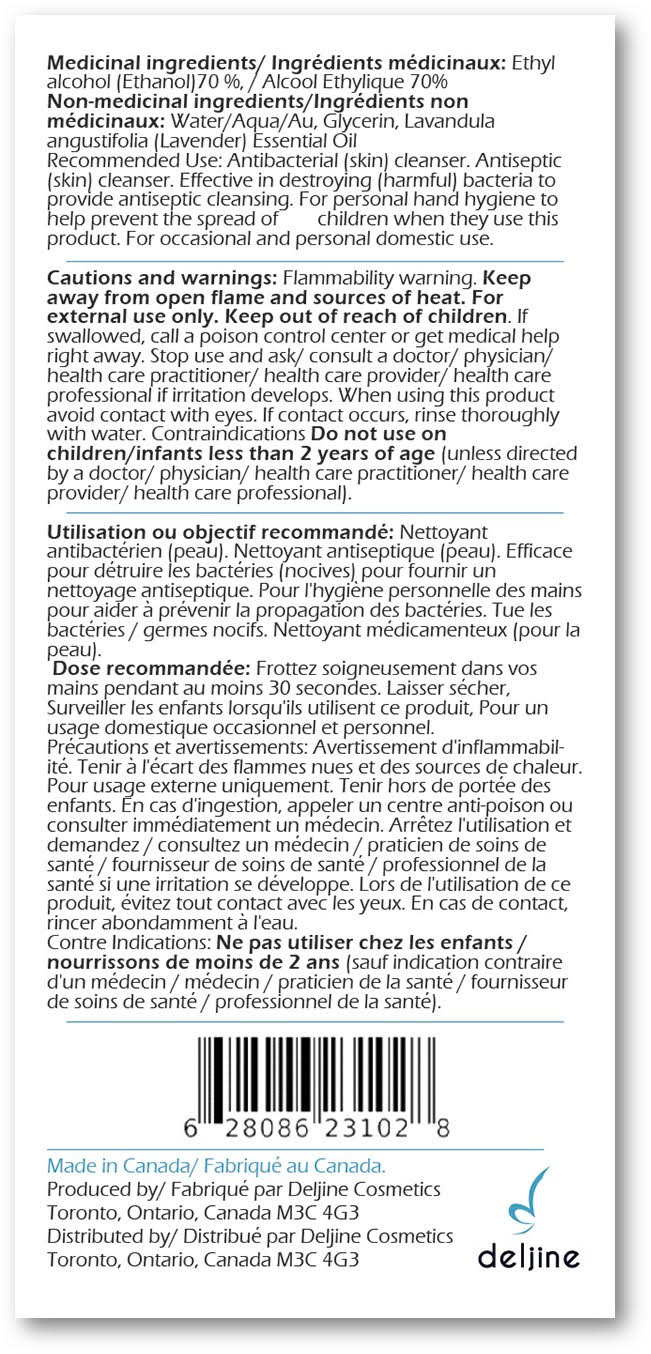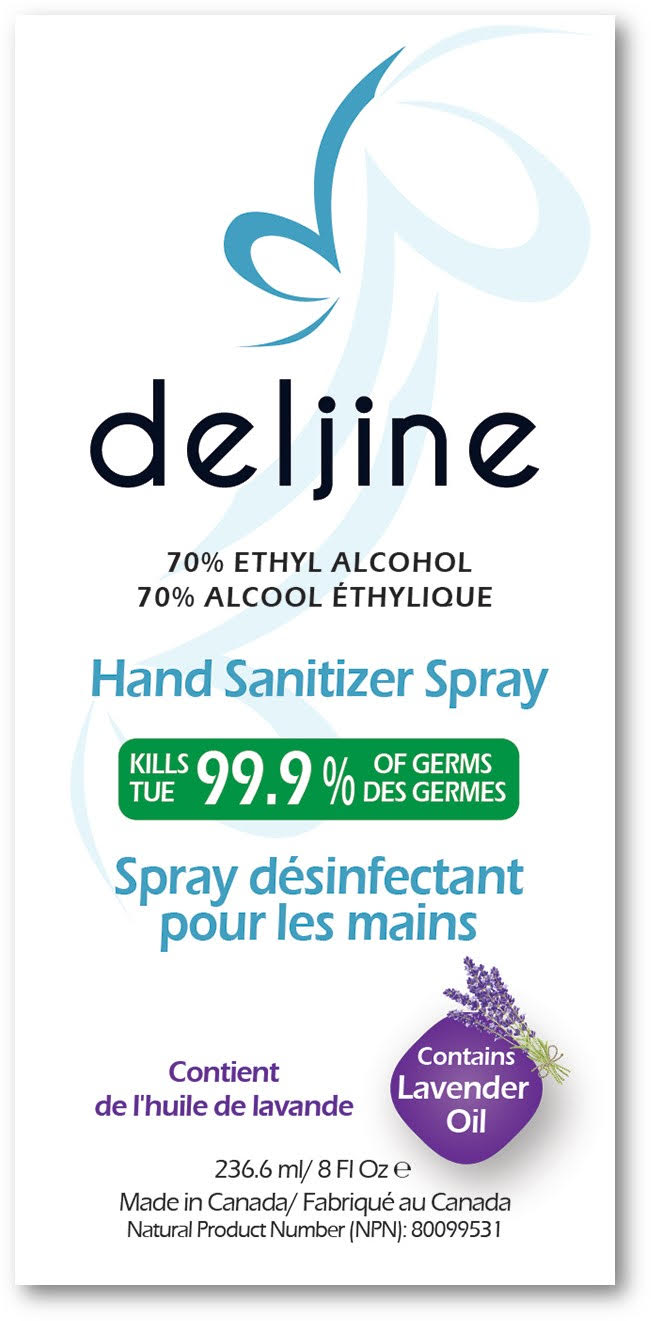 DRUG LABEL: Deljine Hand Sanitizer gel
NDC: 78064-001 | Form: GEL
Manufacturer: Deljine Cosmetics corporation
Category: otc | Type: HUMAN OTC DRUG LABEL
Date: 20200821

ACTIVE INGREDIENTS: ALCOHOL 70 mL/100 mL
INACTIVE INGREDIENTS: GLYCERIN; AMMONIUM ACRYLOYLDIMETHYLTAURATE/BEHENETH-25 METHACRYLATE CROSSPOLYMER (52000 MPA.S); WATER; ALOE VERA LEAF; .ALPHA.-TOCOPHEROL ACETATE, D-

Hand sanitizer

Active Ingredient(s)

Ethyl alcohol (Ethanol)-70 % V/V / Alcool Ethylique 70% V/V

Purpose

Antibacterial (skin) cleanser. Antiseptic (skin) cleanser. Effective in destroying (harmful) bacteria to provide antiseptic cleansing.

Use

For personal hand hygiene to help prevent the spread of bacteria. Kills harmful bacteria/germs. Medicated (skin) cleanser. For use when soap and water are not available.

RECENT MAJOR CHANGES

For personal hand hygiene to help prevent the spread of bacteria. Kills harmful bacteria/germs. Medicated (skin) cleanser. For use when soap and water are not available.

Warnings

Flammability warning. Keep away from open flame and sources of heat. For external use only.

- Do not use on children/infants less than 2 years of age (unless directed by a doctor/ physician/ health care practitioner/ health care provider/ health care professional). Do not use on open skin wounds

When using this product avoid contact with eyes. If contact occurs, rinse thoroughly with water.

Stop use and ask/ consult a doctor/ physician/ health care practitioner/ health care provider/ health care professional if irritation or rash develops.

Keep out of reach of children. If swallowed, call a poison control center or get medical help right away.

Directions

- Rub thoroughly into hands for at least 30 seconds. Allow to dry. Supervise children when they use this product. For occasional and personal domestic use.

Other information

- Store between 15-30C (59-86F), Avoid freezing and excessive heat above 40C (104F)

Inactive ingredients

Water/ Aqua/Eau , Ammonium Acryloyldimethyltaurate, Glycerin, Aloe Barbadensis Leaf Juice, d-alpha-tochopheryl Acetate, fragrance (green tea coriander and mandarin)/ parfum (thé vert coriandre et mandarine).

Package Label - Principal Display Panel

Hand sanitizer gel 1000 ml, NDC: 78064-001-10

78064-002-02